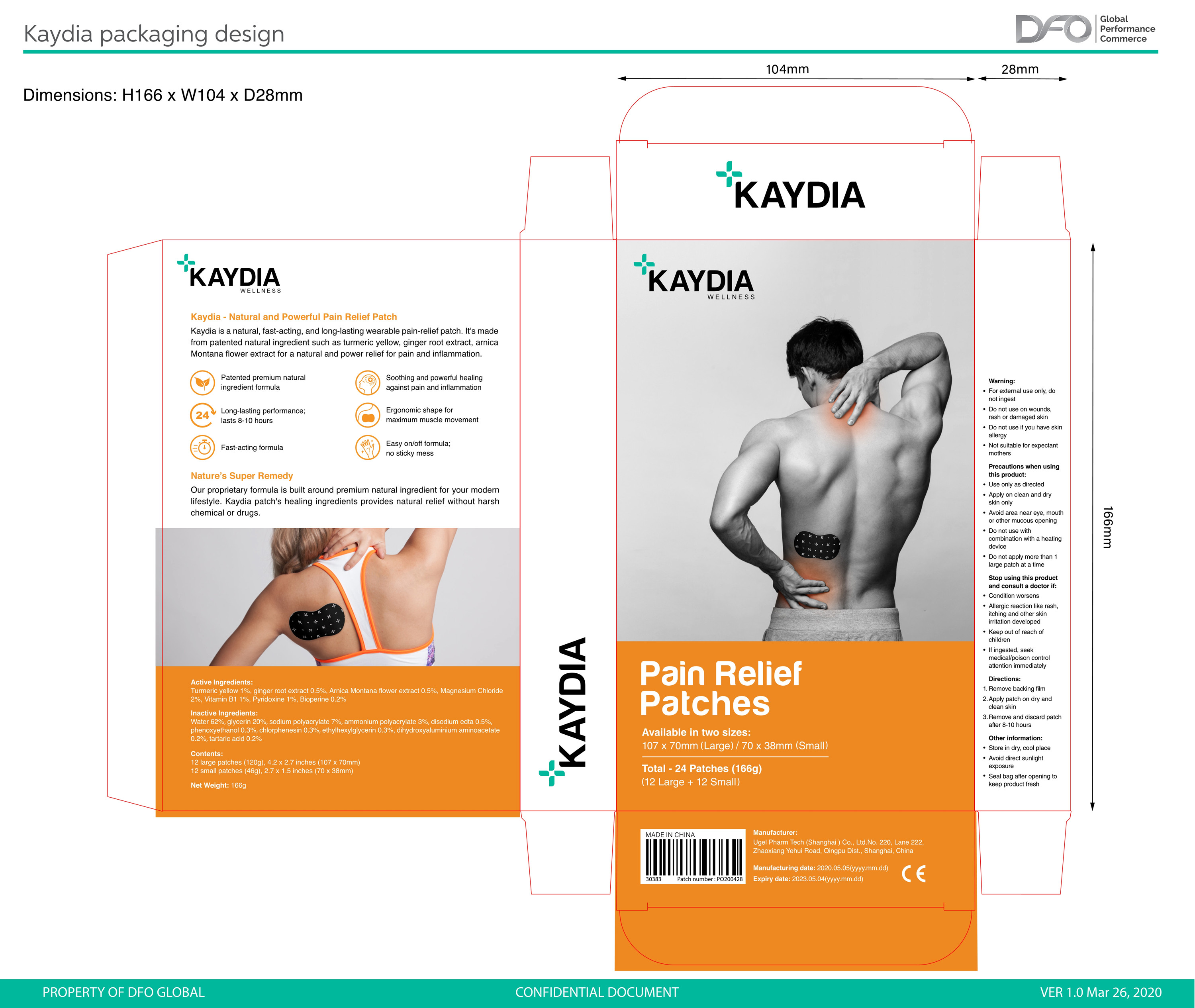 DRUG LABEL: Kaydia Patch
NDC: 75140-001 | Form: PATCH
Manufacturer: Strong Current Enterprises Limited
Category: otc | Type: HUMAN OTC DRUG LABEL
Date: 20200425

ACTIVE INGREDIENTS: GINGER 0.5 g/100 g; ARNICA MONTANA FLOWER 0.5 g/100 g; MAGNESIUM CHLORIDE 2 g/100 g; CURCUMIN 1 g/100 g; THIAMINE 1 g/100 g; PIPERINE 0.2 g/100 g; PYRIDOXINE 1 g/100 g
INACTIVE INGREDIENTS: ETHYLHEXYLGLYCERIN; DIHYDROXYALUMINUM AMINOACETATE; GLYCERIN; PHENOXYETHANOL; CHLORPHENESIN; TARTARIC ACID; WATER; SODIUM POLYACRYLATE (8000 MW); DISODIUM EDTA-COPPER CU-64

Kaydia Patch

Active Ingredients

Turmeric yellow 1%, ginger root extract 0.5%, Arnica Montana flower extract 0.5%, Magnesium Chloride
2%, Vitamin B1 1%, Pyridoxine 1%, Bioperine 0.2%

Warning

For external use only, do not ingest

Do not use on wounds,rash or damaged skin

Do not use if you have skin allergy

Not suitable for expectant mothers.

when using this product

Use only as directed
Apply on clean and dry skin only
Avoid area near eye, mouth or other mucous opening
Do not use with combination with a heating device
Do not apply more than 1 large patch at a time

STOP USE

Stop using this product and consult a doctor if:
Condition worsens
Allergic reaction like rash,itching and other skin irritation developed
Keep out of reach of children

If ingested, seek medical/poison control attention immediately

Directions

1.Remove backing film
2.Apply patch on dry and clean skin
3.Remove and discard patch after 8-10 hours

Other information

Store in dry, cool place

Avoid direct sunlight exposure

Seal bag after opening to keep product fresh

Inactive Ingredients

Water 62%, glycerin 20%, sodium polyacrylate 7%,ammonium polyacrylate 3%, disodium edta 0.5%,phenoxyethanol 0.3%,
chlorphenesin 0.3%, ethylhexylglycerin 0.3%,dihydroxyaluminium aminoacetate 0.2%,tartaric acid 0.2%.